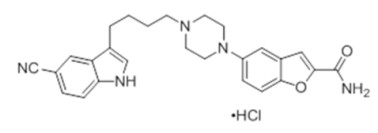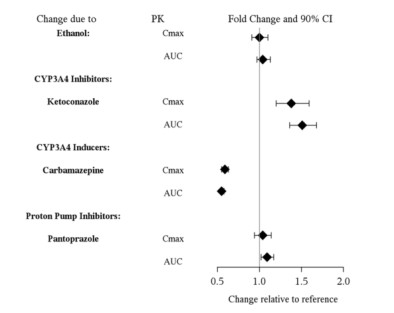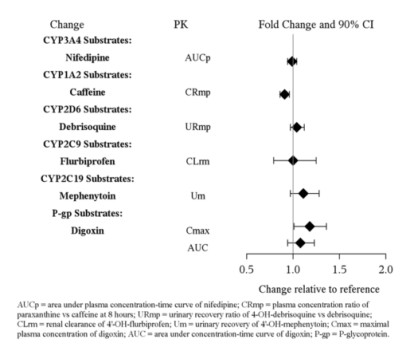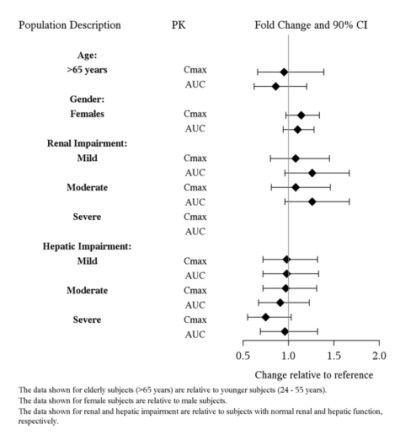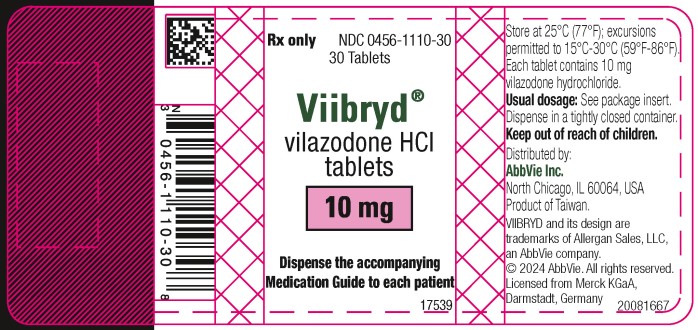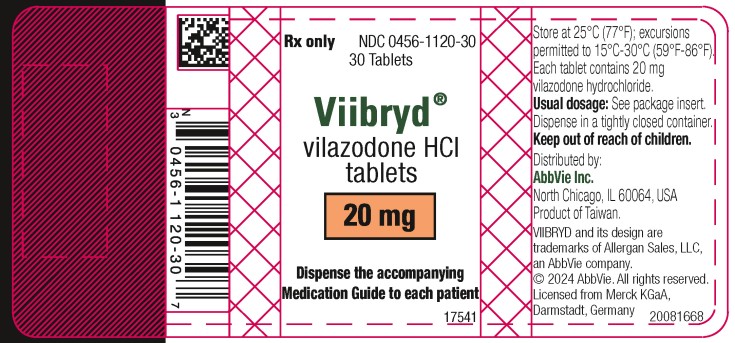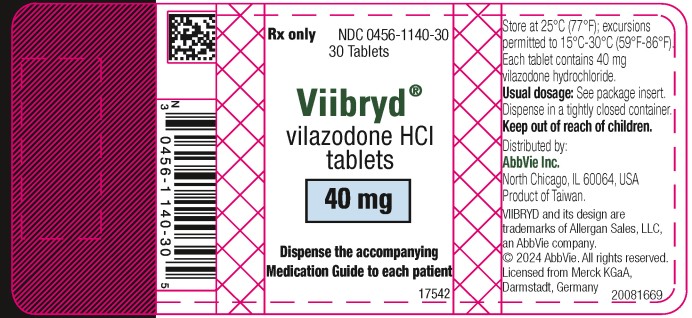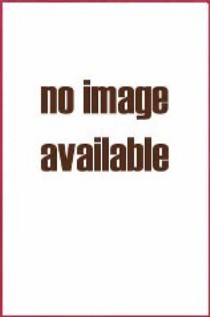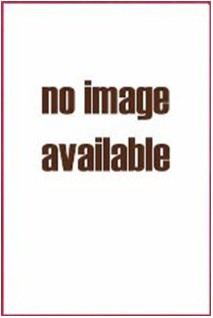 DRUG LABEL: VIIBRYD
NDC: 0456-1110 | Form: TABLET
Manufacturer: Allergan, Inc.
Category: prescription | Type: HUMAN PRESCRIPTION DRUG LABEL
Date: 20231001

ACTIVE INGREDIENTS: VILAZODONE HYDROCHLORIDE 10 mg/1 1
INACTIVE INGREDIENTS: SILICON DIOXIDE; LACTOSE MONOHYDRATE; MAGNESIUM STEARATE; CELLULOSE, MICROCRYSTALLINE; POLYETHYLENE GLYCOL, UNSPECIFIED; POLYVINYL ALCOHOL, UNSPECIFIED; TALC; TITANIUM DIOXIDE; FD&C RED NO. 40

HIGHLIGHTS OF PRESCRIBING INFORMATION

These highlights do not include all the information needed to use VIIBRYD® safely and effectively. See full prescribing information for VIIBRYD.
VIIBRYD (vilazodone hydrochloride) tablets, for oral use
Initial U.S. Approval: 2011

RECENT MAJOR CHANGES

Warnings and Precautions (5.2, 5.3) | 8/2023

WARNING: SUICIDAL THOUGHTS AND BEHAVIORS

See full prescribing information for complete boxed warning.

- Antidepressants increase the risk of suicidal thoughts and behaviors in pediatric and young adult patients (5.1).
- Closely monitor all antidepressant-treated patients for clinical worsening and emergence of suicidal thoughts and behaviors (5.1).
- Viibryd is not approved for use in pediatric patients (8.4).

1 INDICATIONS AND USAGE

VIIBRYD is indicated for the treatment of major depressive disorder (MDD) in adults (1).

2 DOSAGE AND ADMINISTRATION

- Recommended target dosage: 20 mg to 40 mg once daily with food (2.1, 12.3)
- To titrate: start with initial dosage of 10 mg once daily for 7 days, followed by 20 mg once daily. The dose may be increased up to 40 mg once daily after a minimum of 7 days between dosage increases (2.1)
- Prior to initiating VIIBRYD, screen for bipolar disorder (2.2, 5.4)
- When discontinuing VIIBRYD, reduce dosage gradually (2.4, 5.5)

3 DOSAGE FORMS AND STRENGTHS

Tablets: 10 mg, 20 mg, and 40 mg (3)

4 CONTRAINDICATIONS

- Concomitant use of monoamine oxidase inhibitors (MAOIs), or use within 14 days of stopping MAOIs (4)

5 WARNINGS AND PRECAUTIONS

- Serotonin Syndrome: Increased risk when co-administered with other serotonergic agents, but also when taken alone. If it occurs, discontinue VIIBRYD and serotonergic agents and initiate supportive treatment (5.2)
- Increased Risk of Bleeding: Concomitant use of aspirin, nonsteroidal anti-inflammatory drugs (NSAIDs), other antiplatelet drugs, warfarin, and other anticoagulants may increase this risk (5.3)
- Activation of Mania/Hypomania: Screen patients for bipolar disorder (5.4)
- Seizures: Can occur with treatment. Use with caution in patients with a seizure disorder (5.6)
- Angle Closure Glaucoma: Avoid use of antidepressants, including VIIBRYD, in patients with untreated anatomically narrow angles (5.7)
- Sexual Dysfunction: VIIBRYD may cause symptoms of sexual dysfunction (5.9)

6 ADVERSE REACTIONS

Most common adverse reactions (incidence ≥ 5% and at least twice the rate of placebo): diarrhea, nausea, vomiting, and insomnia (6).

To report SUSPECTED ADVERSE REACTIONS, contact AbbVie Inc. at 1-800-678-1605 or FDA at 1-800-FDA-1088 or www.fda.gov/medwatch.

7 DRUG INTERACTIONS

- CYP3A4 Inhibitors: The VIIBRYD dose should not exceed 20 mg once daily when co-administered with strong CYP3A4 inhibitors (2.4, 7).
- CYP3A4 Inducers: Consider increasing VIIBRYD dosage by 2-fold, up to 80 mg once-daily over 1 to 2 weeks when used concomitantly with strong CYP3A4 inducers for greater than 14 days (2.4, 7).

8 USE IN SPECIFIC POPULATIONS

- Pregnancy: Third trimester use may increase risk for persistent pulmonary hypertension and withdrawal in the newborn (8.1).

FULL PRESCRIBING INFORMATION

WARNING: SUICIDAL THOUGHTS AND BEHAVIORS

Antidepressants increased the risk of suicidal thoughts and behaviors in pediatric and young adult patients in short-term studies. Closely monitor all antidepressant-treated patients for clinical worsening and for emergence of suicidal thoughts and behaviors [see Warnings and Precautions (5.1)]. VIIBRYD is not approved for use in pediatric patients [see Use in Specific Populations (8.4)].

1 INDICATIONS AND USAGE

VIIBRYD® is indicated for the treatment of major depressive disorder (MDD) in adults [see Clinical Studies (14)].

2 DOSAGE AND ADMINISTRATION

2.1 Dosage for Treatment of Major Depressive Disorder

The recommended target dosage for VIIBRYD is 20 mg to 40 mg orally once daily with food [see Clinical Pharmacology (12.3), Clinical Studies (14)]. To achieve the target dosage, titrate VIIBRYD as follows:

- Start with an initial dosage of 10 mg once daily with food for 7 days,
- Then increase to 20 mg once daily with food.
- The dose may be increased up to 40 mg once daily with food after a minimum of 7 days between dosage increases.

If a dose is missed, it should be taken as soon as the patient remembers. If it is almost time for the next dose, the patient should skip the missed dose and take the next dose at the regular time. Two doses should not be taken at the same time.

2.2 Screen for Bipolar Disorder Prior to Starting VIIBRYD

Prior to initiating treatment with VIIBRYD or another antidepressant, screen patients for a personal or family history of bipolar disorder, mania, or hypomania [see Warnings and Precautions (5.4)].

2.3 Switching to or from a Monoamine Oxidase Inhibitor Antidepressant

At least 14 days must elapse between discontinuation of a monoamine oxidase inhibitor (MAOI) antidepressant and initiation of VIIBRYD. In addition, at least 14 days must elapse after stopping VIIBRYD before starting an MAOI antidepressant [see Contraindications (4), Warnings and Precautions (5.2)].

2.4 Dosage Adjustments with CYP3A4 Inhibitors or Inducers

Patients receiving concomitant CYP3A4 inhibitors:

During concomitant use of a strong CYP3A4 inhibitor (e.g., itraconazole, clarithromycin, voriconazole), the VIIBRYD dose should not exceed 20 mg once daily. The original VIIBRYD dose level, can be resumed when the CYP3A4 inhibitor is discontinued [see Drug Interactions (7)].

Patients receiving concomitant CYP3A4 inducers:

Based on clinical response, consider increasing the dosage of VIIBRYD by 2-fold, up to a maximum 80 mg once daily, over 1 to 2 weeks in patients taking strong CYP3A4 inducers (e.g., carbamazepine, phenytoin, rifampin) for greater than 14 days. If CYP3A4 inducers are discontinued, gradually reduce the VIIBRYD dosage to its original level over 1 to 2 weeks [see Drug Interactions (7)].

2.5 Discontinuing Treatment with VIIBRYD

Adverse reactions may occur upon discontinuation of VIIBRYD [see Warnings and Precautions (5.5)]. A gradual reduction in dosage rather than abrupt cessation is recommended whenever possible. VIIBRYD should be down tapered from the 40 mg once daily dose to 20 mg once daily for 4 days, followed by 10 mg once daily for 3 days. Patients taking VIIBRYD 20 mg once daily should be tapered to 10 mg once daily for 7 days.

3 DOSAGE FORMS AND STRENGTHS

VIIBRYD Tablets are available as 10 mg, 20 mg and 40 mg film-coated tablets.

10 mg pink, oval tablet, debossed with 10 on one side
20 mg orange, oval tablet, debossed with 20 on one side
40 mg blue, oval tablet, debossed with 40 on one side

4 CONTRAINDICATIONS

VIIBRYD is contraindicated in:

- Patients taking, or within 14 days of stopping, monoamine oxidase inhibitors (MAOIs), including MAOIs such as linezolid or intravenous methylene blue, because of an increased risk of serotonin syndrome [see Warnings and Precautions (5.2), Drug Interactions (7)].

5 WARNINGS AND PRECAUTIONS

5.1 Suicidal Thoughts and Behavior in Adolescents and Young Adults

In pooled analyses of placebo-controlled trials of antidepressant drugs (SSRIs and other antidepressant classes) that included approximately 77,000 adult patients, and over 4,500 pediatric patients, the incidence of suicidal thoughts and behaviors in antidepressant-treated patients age 24 years and younger was greater in antidepressant-treated patients than in placebo-treated patients. There was considerable variation in risk of suicidal thoughts and behaviors among drugs, but there was an increased risk identified in young patients for most drugs studied. There were differences in absolute risk of suicidal thoughts and behaviors across the different indications, with the highest incidence in patients with MDD. The drug-placebo differences in the number of cases of suicidal thoughts and behaviors per 1000 patients treated are provided in Table 1.

Table 1: Risk Differences of the Number of Patients with Suicidal Thoughts or Behaviors in the Pooled Placebo-Controlled Trials of Antidepressants in Pediatric and Adult Patients
Age Range (years) | Drug-Placebo Difference in Number of Patients with Suicidal Thoughts or Behaviors per 1000 Patients Treated
 | Increases Compared to Placebo
<18 | 14 additional patients
18-24 | 5 additional patients
 | Decreases Compared to Placebo
25-64 | 1 fewer patient
≥65 | 6 fewer patients

It is unknown whether the risk of suicidal thoughts and behaviors in children, adolescents, and young adults extends to longer-term use, i.e., beyond four months. However, there is substantial evidence from placebo-controlled maintenance studies in adults with MDD that antidepressants delay the recurrence of depression and that depression itself is a risk factor for suicidal thoughts and behaviors.

Monitor all antidepressant-treated patients for clinical worsening and emergence of suicidal thoughts and behaviors, especially during the initial few months of drug therapy and at times of dosage changes. Counsel family members or caregivers of patients to monitor for changes in behavior and to alert the healthcare provider. Consider changing the therapeutic regimen, including possibly discontinuing VIIBRYD, in patients whose depression is persistently worse, or who are experiencing emergent suicidal thoughts or behaviors.

5.2 Serotonin Syndrome

Serotonin and norepinephrine reuptake inhibitors (SNRIs) and selective serotonin reuptake inhibitor (SSRIs), including VIIBRYD, can precipitate serotonin syndrome, a potentially life-threatening condition. The risk is increased with concomitant use of other serotonergic drugs (including triptans, tricyclic antidepressants, fentanyl, meperidine, methadone, lithium, tramadol, tryptophan, buspirone, amphetamines, and St. John’s Wort) and with drugs that impair metabolism of serotonin, i.e., MAOIs [see Contraindications (4) and Drug Interactions (7)]. Serotonin syndrome can also occur when these drugs are used alone. Symptoms of serotonin syndrome were noted in 0.1% of MDD patients treated with VIIBRYD in premarketing clinical trials.

Serotonin syndrome signs and symptoms may include mental status changes (e.g., agitation, hallucinations, delirium, and coma), autonomic instability (e.g., tachycardia, labile blood pressure, dizziness, diaphoresis, flushing, hyperthermia), neuromuscular symptoms (e.g., tremor, rigidity, myoclonus, hyperreflexia, incoordination), seizures, and gastrointestinal symptoms (e.g., nausea, vomiting, diarrhea).

The concomitant use of VIIBRYD with MAOIs is contraindicated. In addition, do not initiate VIIBRYD in a patient being treated with MAOIs such as linezolid or intravenous methylene blue. No reports involved the administration of methylene blue by other routes (such as oral tablets or local tissue injection). If it is necessary to initiate treatment with an MAOI such as linezolid or intravenous methylene blue in a patient taking VIIBRYD, discontinue VIIBRYD before initiating treatment with the MAOI [see Contraindications (4), Drug Interactions (7.1)].

Monitor all patients taking VIIBRYD for the emergence of serotonin syndrome. Discontinue treatment with VIIBRYD and any concomitant serotonergic agents immediately if the above symptoms occur, and initiate supportive symptomatic treatment. If concomitant use of VIIBRYD with other serotonergic drugs is clinically warranted, inform patients of the increased risk for serotonin syndrome and monitor for symptoms.

5.3 Increased Risk of Bleeding

Drugs that interfere with serotonin reuptake inhibition, including VIIBRYD, increase the risk of bleeding events. Concomitant use of aspirin, nonsteroidal anti-inflammatory drugs (NSAIDs), other antiplatelet drugs, warfarin, and other anticoagulants may add to this risk. Case reports and epidemiological studies (case-control and cohort design) have demonstrated an association between use of drugs that interfere with serotonin reuptake and the occurrence of gastrointestinal bleeding. Based on data from the published observational studies, exposure to SSRIs, particularly in the month before delivery, has been associated with a less than 2-fold increase in the risk of postpartum hemorrhage [see Use in Specific Populations (8.1)]. Bleeding events related to drugs that interfere with serotonin reuptake have ranged from ecchymosis, hematoma, epistaxis, and petechiae to life-threatening hemorrhages.

Inform patients about the increased risk of bleeding associated with the concomitant use of VIIBRYD and antiplatelet agents or anticoagulants. For patients taking warfarin, carefully monitor coagulation indices when initiating, titrating, or discontinuing VIIBRYD.

5.4 Activation of Mania or Hypomania

In patients with bipolar disorder, treating a depressive episode with VIIBRYD or another antidepressant may precipitate a mixed/manic episode. In controlled clinical trials, patients with bipolar disorder were excluded; however, symptoms of mania or hypomania were reported in 0.1% of undiagnosed patients treated with VIIBRYD. Prior to initiating treatment with VIIBRYD, screen patients for any personal or family history of bipolar disorder, mania, or hypomania [see Dosage and Administration (2.2)].

5.5 Discontinuation Syndrome

Adverse reactions after discontinuation of serotonergic antidepressants, particularly after abrupt discontinuation, include: nausea, sweating, dysphoric mood, irritability, agitation, dizziness, sensory disturbances (e.g., paresthesia, such as electric shock sensations), tremor, anxiety, confusion, headache, lethargy, emotional lability, insomnia, hypomania, tinnitus, and seizures. A gradual reduction in dosage rather than abrupt cessation is recommended whenever possible [see Dosage and Administration (2.5)].

5.6 Seizures

VIIBRYD has not been systematically evaluated in patients with a seizure disorder. Patients with a history of seizures were excluded from clinical studies. VIIBRYD should be prescribed with caution in patients with a seizure disorder.

5.7 Angle-Closure Glaucoma

The pupillary dilation that occurs following use of many antidepressant drugs including VIIBRYD may trigger an angle closure attack in a patient with anatomically narrow angles who does not have a patent iridectomy. Avoid use of antidepressants, including VIIBRYD, in patients with untreated anatomically narrow angles.

5.8 Hyponatremia

Hyponatremia may occur as a result of treatment with SNRIs and SSRIs, including VIIBRYD. Cases of serum sodium lower than 110 mmol/L have been reported. Signs and symptoms of hyponatremia include headache, difficulty concentrating, memory impairment, confusion, weakness, and unsteadiness, which may lead to falls. Signs and symptoms associated with more severe and/or acute cases have included hallucination, syncope, seizure, coma, respiratory arrest, and death. In many cases, this hyponatremia appears to be the result of the syndrome of inappropriate antidiuretic hormone secretion (SIADH).

In patients with symptomatic hyponatremia, discontinue VIIBRYD and institute appropriate medical intervention. Elderly patients, patients taking diuretics, and those who are volume-depleted may be at greater risk of developing hyponatremia with SSRIs and SNRIs [see Use in Specific Populations (8.5)].

5.9 Sexual Dysfunction

Use of SSRIs, including VIIBRYD, may cause symptoms of sexual dysfunction [see Adverse Reactions (6.1)]. In male patients, SSRI use may result in ejaculatory delay or failure, decreased libido, and erectile dysfunction. In female patients, SSRI use may result in decreased libido and delayed or absent orgasm.

It is important for prescribers to inquire about sexual function prior to initiation of VIIBRYD and to inquire specifically about changes in sexual function during treatment, because sexual function may not be spontaneously reported. When evaluating changes in sexual function, obtaining a detailed history (including timing of symptom onset) is important because sexual symptoms may have other causes, including the underlying psychiatric disorder. Discuss potential management strategies to support patients in making informed decisions about treatment.

6 ADVERSE REACTIONS

The following adverse reactions are discussed in greater detail in other sections of the labeling:

- Suicidal Thoughts and Behaviors in Adolescents and Young Adults [see Warnings and Precautions (5.1)].
- Serotonin Syndrome [see Warnings and Precautions (5.2)].
- Increased Risk of Bleeding [see Warnings and Precautions (5.3)].
- Activation of Mania or Hypomania [see Warnings and Precautions (5.4)].
- Discontinuation Syndrome [see Warnings and Precautions (5.5)].
- Seizures [see Warnings and Precautions (5.6)].
- Angle-Closure Glaucoma [see Warnings and Precautions (5.7)].
- Hyponatremia [see Warnings and Precautions (5.8)].
- Sexual Dysfunction [see Warnings and Precautions (5.9)].

6.1 Clinical Trials Experience

Because clinical trials are conducted under widely varying conditions and varying lengths of time, adverse reaction rates observed in the clinical trials of a drug cannot be directly compared to rates in the clinical studies of another drug and may not reflect rates observed in practice.

The most commonly observed adverse reactions in VIIBRYD-treated patients with major depressive disorder (MDD) in placebo-controlled studies (incidence ≥ 5% and at least twice the rate of placebo) were diarrhea, nausea, vomiting, and insomnia.

Patient Exposure

The safety of VIIBRYD was evaluated in 3,007 patients (18-70 years of age) diagnosed with MDD who participated in clinical studies, representing 676 patient-years of exposure. In an open-label 52 week study at 40 mg daily, 599 patients were exposed to VIIBRYD for a total of 348 patient-years.

The adverse reaction information presented below was derived from studies of VIIBRYD 20 mg and 40 mg daily in patients with MDD including:

- Four placebo-controlled 8 to 10-week studies in 2,233 patients, including 1,266 VIIBRYD-treated patients; and
- An open-label 52-week study of 599 VIIBRYD-treated patients.

These studies included a titration period of 10 mg daily for 7 days, followed by 20 mg daily for 7 days or to 40 mg daily over 2 weeks. In these clinical trials, VIIBRYD was administered with food.

Adverse reactions reported as reasons for discontinuation of treatment

In these studies, 7.3% of the VIIBRYD-treated patients discontinued treatment due to an adverse reaction, compared with 3.5% of placebo-treated patients. The most common adverse reaction leading to discontinuation in at least 1% of the VIIBRYD-treated patients in the placebo-controlled studies was nausea (1.4%).

Common adverse reactions in placebo-controlled MDD studies

Table 2 shows the incidence of common adverse reactions occurring in ≥ 2% of VIIBRYD-treated patients and greater than the rate of placebo-treated patients in MDD Studies. There were no dose-related adverse reactions between 20 mg and 40 mg reported.

Table 2: Common Adverse Reactions Occurring in ≥ 2% of VIIBRYD-treated Patients and Greater than the Rate of Placebo-Treated Patients
System Organ Class Preferred Term | Placebo N=967 | VIIBRYD 20 mg/day N=288 | VIIBRYD 40 mg/day N=978
Gastrointestinal disorders
Diarrhea | 10% | 26% | 29%
Nausea | 7% | 22% | 24%
Dry mouth | 5% | 8% | 7%
Vomiting | 2% | 4% | 5%
Abdominal pain^1 | 3% | 7% | 4%
Dyspepsia | 2% | 2% | 3%
Flatulence | 1% | 3% | 3%
Gastroenteritis | 1% | 1% | 2%
Abdominal distension | 1% | 2% | 1%
Nervous system disorders
Headache^2 | 14% | 15% | 14%
Dizziness | 5% | 6% | 8%
Somnolence | 2% | 4% | 5%
Paresthesia | 1% | 1% | 2%
Psychiatric disorders
Insomnia | 2% | 7% | 6%
Abnormal dreams | 2% | 2% | 3%
Restlessness^3 | 1% | 2% | 3%
General disorders
Fatigue | 3% | 4% | 3%
Cardiac disorders
Palpitations | <1% | 1% | 2%
Metabolism and nutrition disorders
Increased appetite | 1% | 1% | 3%
Musculoskeletal and connective tissue disorders
Arthralgia | 1% | 2% | 1%
Investigations
Increased weight | 1% | 1% | 2%

^1 Includes abdominal discomfort, abdominal pain upper, and abdominal pain.

^2 Includes headache and tension headache

^3 Includes restlessness, akathisia, and restless legs syndrome

Sexual adverse reactions are presented in Table 3

Sexual adverse reactions

Table 3 displays the most common sexual adverse reactions in the placebo-controlled MDD studies.

Table 3: Common Sexual Adverse Reactions Occurring in ≥ 2% of VIIBRYD-treated Patients and Greater than the Rate of Placebo-Treated Patients
Preferred Term | Males |  |  | Females
 | Placebo N=416 | VIIBRYD 20 mg/day N=122 | VIIBRYD 40 mg/day N=417 | Placebo N=551 | VIIBRYD 20 mg/day N=166 | VIIBRYD 40 mg/day N=561
Abnormal Orgasm* | <1% | 2% | 2% | 0% | 1% | 1%
Erectile dysfunction | 1% | 0% | 3% | − | − | −
Libido decreased | <1% | 3% | 4% | <1% | 2% | 2%
Ejaculation disorder | 0% | 1% | 2% | − | − | −

− Not applicable

* Includes abnormal orgasm and anorgasmia

Other adverse reactions observed in clinical studies

The following list does not include reactions: 1) already listed in previous tables or elsewhere in labeling, 2) for which a drug cause was remote, 3) which were so general as to be uninformative, 4) which were not considered to have significant clinical implications, or 5) which occurred at a rate equal to or less than placebo.

Reactions are categorized by body system according to the following definitions: frequent adverse reactions are those occurring in at least 1/100 patients; infrequent adverse reactions are those occurring in 1/100 to 1/1000 patients; rare reactions are those occurring in fewer than 1/1000 patients:

Cardiac disorders: infrequent: ventricular extrasystoles

Eye disorders: infrequent: dry eye, vision blurred, rare: cataracts

Nervous System: frequent: sedation, tremor; infrequent: migraine

Psychiatric disorders: infrequent: panic attack

Skin and subcutaneous tissue disorders: infrequent: hyperhidrosis, night sweats

6.2 Postmarketing Experience

The following adverse reactions have been identified during post-approval use of VIIBRYD. Because these reactions are reported voluntarily from a population of uncertain size, it is not always possible to estimate their frequency or establish a causal relationship to drug exposure. Reports of adverse reactions temporally associated with VIIBRYD that have been received since market introduction and that are not listed above include the following:

General Disorders and Administration Site Conditions: irritability
Nervous System Disorders: sleep paralysis
Psychiatric Disorders: hallucinations, suicide attempt, suicidal ideation
Skin and subcutaneous tissue disorders: rash, generalized rash, urticaria, drug eruption
Gastrointestinal System: acute pancreatitis
Respiratory, Thoracic and Mediastinal Disorders: anosmia, hyposmia

7 DRUG INTERACTIONS

7.1 Drugs Having Clinically Important Interactions With VIIBRYD

Table 4: Clinically Important Drug Interactions with VIIBRYD
Concomitant Drug Name or Drug Class | Clinical Rationale | Clinical Recommendation
Monoamine Oxidase Inhibitors (MAOIs) | The concomitant use of MAOIs and serotonergic drugs including VIIBRYD increases the risk of serotonin syndrome. | VIIBRYD is contraindicated in patients taking MAOIs, including MAOIs such as linezolid or intravenous methylene blue [see Contraindications (4), Dosage and Administration (2.3), and Warnings and Precautions (5.2)].
Other Serotonergic Drugs | Concomitant use of VIIBRYD with other serotonergic drugs (including other SSRIs, SNRIs, triptans, tricyclic antidepressants, opioids, lithium, buspirone, amphetamines, tryptophan, and St. John's Wort) increases the risk of serotonin syndrome. | Monitor patients for signs and symptoms of serotonin syndrome, particularly during VIIBRYD initiation. If serotonin syndrome occurs, consider discontinuation of VIIBRYD and/or concomitant serotonergic drugs [see Warnings and Precautions (5.2)].
Antiplatelet Agents and Anticoagulants | Serotonin release by platelets plays an important role in hemostasis. The concurrent use of an antiplatelet agent or anticoagulant with VIIBRYD may potentiate the risk of bleeding. | Inform patients of the increased risk of bleeding with the concomitant use of VIIBRYD and antiplatelet agents and anticoagulants. For patients taking warfarin, carefully monitor the international normalized ratio (INR) when initiating, titrating, or discontinuing VIIBRYD [see Warnings and Precautions (5.3)].
Strong CYP3A4 Inhibitors (e.g., itraconazole, clarithromycin, voriconazole) | The concomitant use of VIIBRYD and strong CYP3A4 inhibitors increased the exposure of vilazodone compared to the use of VIIBRYD alone [see Clinical Pharmacology (12.3)]. | The VIIBRYD dose should not exceed 20 mg once daily with the concomitant use of a strong CYP3A4 inhibitor [see Dosage and Administration (2.4), Clinical Pharmacology (12.3)].
Strong CYP3A4 Inducers (e.g., carbamazepine, phenytoin, rifampin) | The concomitant use of VIIBRYD and strong CYP3A4 inducers decreased the exposure of vilazodone compared to the use of VIIBRYD alone [see Clinical Pharmacology (12.3)]. | Based on clinical response, consider increasing the dosage of VIIBRYD, over 1 to 2 weeks in patients taking strong CYP3A4 inducers for greater than 14 days [see Dosage and Administration (2.4), Clinical Pharmacology (12.3)].
Digoxin | Digoxin is a narrow therapeutic index drug. Concomitant use of VIIBRYD increased digoxin concentrations [see Clinical Pharmacology (12.3)]. | Measure serum digoxin concentrations before initiating concomitant use of VIIBRYD. Continue monitoring and reduce digoxin dose as necessary.

7.2 Drugs Having No Clinically Important Interactions With VIIBRYD

Based on pharmacokinetic studies, no dosage adjustment is required for drugs that are substrates of CYP1A2, CYP2B6, CYP2C9, CYP2C19, CYP2D6, CYP3A4, and/or P-glycoprotein (except narrow therapeutic index drugs, e.g., digoxin), when VIIBRYD is administered concomitantly [see Drug Interactions (7.1), Clinical Pharmacology (12.3)].

8 USE IN SPECIFIC POPULATIONS

8.1 Pregnancy

Pregnancy Exposure Registry

There is a pregnancy exposure registry that monitors pregnancy outcomes in women exposed to antidepressants during pregnancy. Healthcare providers are encouraged to advise patients to register by calling the National Pregnancy Registry for Antidepressants at 1-844-405-6185 or visiting online at https://womensmentalhealth.org/research/pregnancyregistry/antidepressants.

Risk Summary

Based on data from published observational studies, exposure to SSRIs, particularly in the month before delivery, has been associated with a less than 2-fold increase in the risk of postpartum hemorrhage [see Warnings and Precautions (5.3) and Clinical Considerations].

There are no adequate and well-controlled studies of VIIBRYD in pregnant women. The background risk of major birth defects and miscarriage for the indicated population is unknown. However, the background risk in the U.S. general population of major birth defects is 2-4% and of miscarriage is 15-20% of clinically recognized pregnancies. In animal reproduction studies, oral administration of vilazodone during the period of organogenesis at doses up to 48 and 17 times the maximum recommended human dose (MRHD) in rats and rabbits, respectively, resulted in decreased fetal body weight gain and delayed skeletal ossification but no teratogenic effects were observed. Decreased fetal body weight and delayed skeletal ossification were not observed at doses up to 10 and 4 times the MRHD in rats and rabbits, respectively [see Data].

Clinical Considerations

Disease-associated maternal and/or embryo/fetal risk

A prospective, longitudinal study followed 201 pregnant women with a history of major depressive disorder who were euthymic and taking antidepressants at the beginning of pregnancy. The women who discontinued antidepressants during pregnancy were more likely to experience a relapse of major depression than women who continued antidepressants. Consider the risks of untreated depression when discontinuing or changing treatment with antidepressant medication during pregnancy and postpartum.

Maternal Adverse Reactions

Use of VIIBRYD in the month before delivery may be associated with an increased risk of postpartum hemorrhage [see Warnings and Precautions (5.3)].

Fetal/Neonatal adverse reactions

Exposure to SSRIs and SNRIs, including VIIBRYD, in late pregnancy may lead to an increased risk for neonatal complications requiring prolonged hospitalization, respiratory support, and tube feeding, and/or persistent pulmonary hypertension of the newborn (PPHN). Monitor neonates who were exposed to VIIBRYD in the third trimester of pregnancy for PPHN and drug discontinuation syndrome [see Data].

Data

Human Data

Third Trimester Exposure

Neonates exposed to SSRIs or SNRIs late in the third trimester, have developed complications requiring prolonged hospitalization, respiratory support, and tube feeding. These findings are based on post-marketing reports. Such complications can arise immediately upon delivery. Reported clinical findings have included respiratory distress, cyanosis, apnea, seizures, temperature instability, feeding difficulty, vomiting, hypoglycemia, hypotonia, hypertonia, hyperreflexia, tremor, jitteriness, irritability, and constant crying. These features are consistent with either a direct toxic effect of SSRIs and SNRIs or, possibly, a drug discontinuation syndrome. In some cases, the clinical picture was consistent with serotonin syndrome [see Warnings and Precautions (5.2)].

Exposure during late pregnancy to SSRIs may have an increased risk for persistent pulmonary hypertension of the newborn (PPHN). PPHN occurs in 1-2 per 1,000 live births in the general population and is associated with substantial neonatal morbidity and mortality. In a retrospective case-control study of 377 women whose infants were born with PPHN and 836 women whose infants were born healthy, the risk for developing PPHN was approximately six-fold higher for infants exposed to SSRIs after the 20th week of gestation compared to infants who had not been exposed to antidepressants during pregnancy. A study of 831,324 infants born in Sweden in 1997-2005 found a PPHN risk ratio of 2.4 (95% CI 1.2-4.3) associated with patient-reported maternal use of SSRIs "in early pregnancy" and a PPHN risk ratio of 3.6 (95% CI 1.2-8.3) associated with a combination of patient-reported maternal use of SSRIs "in early pregnancy" and an antenatal SSRI prescription "in later pregnancy."

Animal Data

No teratogenic effects were observed when vilazodone was given to pregnant rats or rabbits during the period of organogenesis at oral doses up to 200 and 36 mg/kg/day, respectively. These doses are 48 and 17 times, in rats and rabbits, respectively, the maximum recommended human dose (MRHD) of 40 mg on a mg/m^2 basis. Fetal body weight gain was reduced, and skeletal ossification was delayed in both rats and rabbits at these doses; these effects were not observed at doses up to 10 times the MRHD in rats or 4 times the MRHD in rabbits.

When vilazodone was administered to pregnant rats at an oral dose of 30 times the MRHD during the period of organogenesis and throughout pregnancy and lactation, the number of live born pups was decreased. There was an increase in early postnatal pup mortality, and among surviving pups there was decreased body weight, delayed maturation, and decreased fertility in adulthood. There was some maternal toxicity at this dose. These effects were not seen at 6 times the MRHD.

8.2 Lactation

Risk Summary

There are no data on the presence of vilazodone in human milk, the effects of vilazodone on the breastfed infant, or the effects of the drug on milk production. However, vilazodone is excreted in rat milk [see Data]. The developmental and health benefits of breastfeeding should be considered along with the mother’s clinical need for VIIBRYD and any potential adverse effects on the breastfed child from VIIBRYD or from the underlying maternal condition.

Data

Animal Data

Administration of vilazodone to lactating rats at an oral dose of 30 times the maximum recommended human dose (MRHD), resulted in early postnatal pup mortality, and among surviving pups there was decreased body weight and delayed maturation.

8.4 Pediatric Use

The safety and effectiveness of VIIBRYD have not been established in pediatric patients for the treatment of MDD.

Efficacy was not demonstrated in two adequate and well controlled, 8-week studies including a total of 1002 pediatric patients ages 7 years to 17 years of age with MDD. The following adverse reactions were reported in at least 5% of pediatric patients treated with VIIBRYD and occurred at a rate at least twice that for pediatric patients receiving placebo: nausea, vomiting, diarrhea, abdominal pain/discomfort, and dizziness.

Antidepressants increased the risk of suicidal thoughts and behaviors in pediatric patients [see Boxed Warning, Warnings and Precautions (5.1), and Adverse Reactions (6.2)].

Juvenile Animal Toxicity Data

In a juvenile animal study, male and female rats were treated with vilazodone (10, 50, and 200 mg/kg/day) starting on postnatal day (PND) 21 through 90. A delay in the age of attainment of vaginal patency (i.e. sexual maturation) was observed in females starting at 50 mg/kg/day with a No Observed Adverse Effect Level (NOAEL) of 10 mg/kg/day. This NOAEL was associated with AUC levels similar to those measured at a maximum dose tested in pediatrics (30 mg). Adverse behavioral effects (lack of habituation in an acoustic startle test) were observed in males at 200 mg/kg and females starting at 50 mg/kg both during drug treatment and the recovery periods. The NOAEL for this finding was 50 mg/kg for males and 10 mg/kg for females, which was associated with AUC levels greater than (males) or similar (females), to those observed with the maximum dose tested in pediatric patients. An 8% decrease in femur mineral density was observed in female rats at 200 mg/kg, compared to the control group. The NOAEL for this finding was 50 mg/kg, which was associated with an AUC level greater than those measured at the maximum dose tested in pediatrics.

8.5 Geriatric Use

Based on a pharmacokinetic study, no dosage adjustment of VIIBRYD is recommended on the basis of age (see Figure 3). Results from pharmacokinetic study of a single 20 mg VIIBRYD dose in geriatric subjects (> 65 years-old) vs. younger subjects (24-55 years-old) demonstrated that the pharmacokinetics were generally similar between the two age groups [see Clinical Pharmacology (12.3)].

Clinical studies of VIIBRYD did not include sufficient numbers of subjects aged 65 and over to determine whether they respond differently from younger subjects. Of the 3,007 patients in clinical studies with VIIBRYD, 65 (2.2%) were 65 years of age or older, and 378 (12.6%) were 55 to 64 years of age. In general, dose selection for an elderly patient should be conservative, usually starting at the low end of the dosing range, reflecting the greater frequency of decreased hepatic, renal, or cardiac function, and of concomitant disease or other drug therapy.

Serotonergic antidepressants have been associated with cases of clinically significant hyponatremia in elderly patients, who may be at greater risk for this adverse reaction [see Warnings and Precautions (5.8)]. No other differences in adverse reactions were observed between geriatric and younger patients.

8.6 Use in Other Patient Populations

No dosage adjustment of VIIBRYD is necessary on the basis of gender, renal function (mild to severe renal impairment, glomerular filtration rate: 15-90 mL/minute), or hepatic function (mild to severe hepatic impairment, Child-Pugh score: 5-15 [see Clinical Pharmacology (12.3)].

9 DRUG ABUSE AND DEPENDENCE

9.1 Controlled Substance

VIIBRYD is not a controlled substance.

9.2 Abuse and Dependence

VIIBRYD has been systematically studied in animals and did not demonstrate abuse or dependence potential. While VIIBRYD has not been systematically studied in humans for its potential for abuse, there was no suggested evidence of drug-seeking behavior in the clinical studies.

10 OVERDOSAGE

There is limited clinical trial experience regarding human overdose with VIIBRYD. The adverse reactions associated with overdose of VIIBRYD at doses of 200-280 mg (5 to 7 times the recommended dosage) as observed in clinical trials included serotonin syndrome, lethargy, restlessness, hallucinations, and disorientation.

For current information on the management of poisoning or overdose, contact a poison control center at 1-800-222-1222.

No specific antidotes for vilazodone are known. Removal of vilazodone by dialysis has not been studied; however, the high volume of distribution of vilazodone suggests that dialysis will not be effective in reducing vilazodone plasma concentrations.

11 DESCRIPTION

VIIBRYD tablets for oral administration contain polymorph Form IV vilazodone hydrochloride (HCl), a selective serotonin reuptake inhibitor and a 5HT1A receptor partial agonist.

Vilazodone HCl is 2-benzofurancarboxamide, 5-[4-[4-(5-cyano-1H-indol-3-yl)butyl]-1-piprazinyl]-, hydrochloride (1:1). Its molecular weight is 477.99. The structural formula is:

VIIBRYD tablets are available as 10 mg, 20 mg, and 40 mg film-coated tablets containing 10 mg, 20 mg, and 40 mg of vilazodone HCl, respectively.

In addition to the active ingredient, VIIBRYD tablets contain the following inactive ingredients: colloidal silicon dioxide, lactose monohydrate, magnesium stearate, microcrystalline cellulose, polyethylene glycol, polyvinyl alcohol, talc, titanium dioxide, FD&C Blue #1 (40 mg only), FD&C Red #40 (10 mg only), and FD&C Yellow #6 (20 mg only).

12 CLINICAL PHARMACOLOGY

12.1 Mechanism of action

The mechanism of action of vilazodone in the treatment of major depressive disorder is not fully understood, but is thought to be related to its enhancement of serotonergic activity in the CNS through selective inhibition of serotonin reuptake. Vilazodone is also a partial agonist at serotonergic 5-HT1A receptors; however, the net result of this action on serotonergic transmission and its role in vilazodone’s antidepressant effect are unknown.

12.2 Pharmacodynamics

Vilazodone binds with high affinity to the serotonin reuptake site (Ki= 0.1 nM), but not to the norepinephrine (Ki=56 nM) or dopamine (Ki=37 nM) reuptake sites. Vilazodone potently and selectively inhibits reuptake of serotonin (IC50= 1.6 nM). Vilazodone also binds selectively with high affinity to 5-HT1A receptors (IC50=2.1 nM) and is a 5-HT1A receptor partial agonist.

Cardiac Electrophysiology

Treatment with VIIBRYD did not prolong the QTc interval. The effect of VIIBRYD [20, 40, 60, and 80 mg (2 times the recommended dosage)] on the QTc interval was evaluated in a randomized, placebo-, and active-controlled (moxifloxacin 400 mg), parallel-group, thorough QTc study in 157 healthy subjects. The study demonstrated an ability to detect small effects. The upper bound of the 90% confidence interval for the largest placebo-adjusted, baseline-corrected QTc interval was below 10 msec, based on the individual correction method (QTcI). Thus, at doses of 2 times the recommended dosage, VIIBRYD did not prolong the QTc interval to a clinically relevant extent.

12.3 Pharmacokinetics

Vilazodone activity is due primarily to the parent drug. The pharmacokinetics of vilazodone (5 mg – 80 mg) are dose-proportional. Accumulation of vilazodone after administration of single VIIBRYD doses did not vary with dose, and steady-state was achieved in about 3 days. Elimination of vilazodone is primarily by hepatic metabolism with a terminal half-life of approximately 25 hours. At steady-state, after daily dosing of VIIBRYD 40 mg under fed conditions, the mean Cmax value was 156 ng/mL, and the mean AUC (0-24 hours) value was 1645 ng·h/mL.

Absorption

Vilazodone concentrations peaked at a median of 4-5 hours (Tmax) after VIIBRYD administration and declined with a terminal half-life of approximately 25 hours. The absolute bioavailability of vilazodone was 72% with food.Vilazodone AUC and Cmax in the fasted state can be decreased by approximately 50% and 60%, respectively, compared to the fed state. Administration without food can result in inadequate drug concentrations and may reduce effectiveness.

Coadministration of VIIBRYD with ethanol or with a proton pump inhibitor (pantoprazole) did not affect the rate or extent of vilazodone absorption. In addition, neither the Tmax nor terminal elimination rate of vilazodone was altered by coadministration with either pantoprazole or ethanol.

Absorption is decreased by approximately 25% if vomiting occurs within 7 hours of ingestion; no replacement dose is needed.

Distribution

Vilazodone is widely distributed and approximately 96-99% protein-bound. Administration of VIIBRYD to a patient taking another drug that is highly protein bound may cause increased free concentrations of the other drug, because vilazodone is highly bound to plasma protein. The interaction between vilazodone and other highly protein-bound drugs has not been evaluated.

Metabolism and Elimination

VIIBRYD is extensively metabolized through CYP and non-CYP pathways (possibly by carboxylesterase), with only 1% of the dose recovered in the urine and 2% of the dose recovered in the feces as unchanged vilazodone. CYP3A4 is primarily responsible for its metabolism among CYP pathways, with minor contributions from CYP2C19 and CYP2D6.

Drug Interaction Studies

Figure 1 below includes the impact of other drugs on the pharmacokinetics of vilazodone [see Drug Interactions (7)].

Figure 1. Effect of Other Drugs on Vilazodone Pharmacokinetics

In vitro studies indicate that vilazodone is unlikely to inhibit or induce the metabolism of substrates for CYP1A1, 1A2, 2A6, 2B6, 2C9, 2C19, 2D6, 2E1, 3A4 or 3A5, except for CYP2C8. The effect of vilazodone on CYP2C8 activity has not been tested in vivo. Figure 2 below includes the impact of vilazodone on the pharmacokinetics of other drugs in vivo.

Figure 2. Impact of Vilazodone on Other Drug Pharmacokinetics

Studies in Specific Populations:

The presence of mild to severe renal impairment or mild to severe hepatic impairment did not affect the apparent clearance of vilazodone (see Figure 3). There were no pharmacokinetic differences of vilazodone in geriatric patients compared to younger patients, or between males and females (see Figure 3).

Figure 3: Impact of Intrinsic Factors on Vilazodone Pharmacokinetics

13 NONCLINICAL TOXICOLOGY

13.1 Carcinogenesis, Mutagenesis, Impairment of Fertility

Carcinogenesis

Carcinogenicity studies were conducted in which B6C3F1 mice and Wistar rats were given oral doses of vilazodone up to 135 and 150 mg/kg/day, respectively, for 2 years. These doses are approximately 16.5 and 36 times the maximum recommended human dose (MRHD) of 40 mg, respectively, on a mg/m^2 basis.

In mice, the incidence of hepatocellular carcinomas was increased in males at 16.5 times the MRHD; this finding was not observed at 5.5 times the MRHD. The incidence of malignant mammary gland tumors was numerically increased in females at 5.5 and 16.5 times the MRHD, with statistical significance at 16.5 the MRHD; this finding was not observed at 1.8 times the MRHD. Elevated prolactin levels were observed in a 2-week study of vilazodone administered at 5.5 and 33 times the MRHD. Increases in prolactin levels are known to cause mammary tumors in rodents.

In the rat study, vilazodone was not carcinogenic in either sex at doses up to 36 times the MRHD.

Mutagenesis

Vilazodone was not mutagenic in the in vitro bacterial reverse mutation assay (Ames test). Vilazodone was negative in the in vitro V79/HGRPT mammalian cell forward mutation assay. Vilazodone was clastogenic in two in vitro mammalian cell chromosome aberration assays. However, vilazodone was negative for clastogenic activity in both an in vivo rat bone marrow chromosome aberration assay and a micronucleus test. Vilazodone was also negative in an in vivo/in vitro unscheduled DNA synthesis assay in rats.

Impairment of Fertility

Treatment of rats with vilazodone at a dose of 125 mg/kg, which is 30 times the MRHD of 40 mg on a mg/m^2 basis, caused impairment of male fertility with no effect on female fertility. Impaired male fertility was not observed at 6 times the MRHD.

14 CLINICAL STUDIES

The efficacy of VIIBRYD as a treatment for major depressive disorder was demonstrated in four multicenter, randomized, double-blind, placebo-controlled studies in adult (18-70 years of age) outpatients who met the Diagnostic and Statistical Manual of Mental Disorders (DSM-IV-TR) criteria for MDD. Three 8-week studies evaluated the efficacy of VIIBRYD 40 mg (Studies 1-3) and one 10-week study (Study 4) evaluated the efficacy of VIIBRYD 20 mg and 40 mg (see Table 5). In these studies, patients were randomized to either 20 mg or 40 mg, or placebo once daily with food. Patients were either titrated over 1 week to a dose of 20 mg daily or over 2 weeks to a dose of 40 mg once daily of VIIBRYD with food. VIIBRYD was superior to placebo in the improvement of depressive symptoms as measured by the change from baseline to endpoint visit in the Montgomery-Asberg Depression Rating Scale (MADRS) total score for both doses. The MADRS is a ten-item, clinician-rated scale used to assess severity of depressive symptoms. Scores on the MADRS range from 0 to 60, with higher scores indicating more severe depression. Clinical Global Impression - Severity (CGI-S) was evaluated in Studies 3 and 4. VIIBRYD 20 mg and 40 mg demonstrated superiority over placebo as measured by improvement in CGI-S score.

Table 5: Summary of Results for the Primary Efficacy Endpoint - MADRS Total Score
Study Number | Treatment Group | Number of Patients a | Mean Baseline Score (SD) | LS Mean Change from Baseline (SE) | Placebo-subtracted Difference b (95% CI)
Study 1 | VIIBRYD 40 mg/day | 198 | 30.8 (3.90) | -12.9 (0.77) | -3.2 (-5.2, -1.3)
 | Placebo | 199 | 30.7 (3.93) | -9.6 (0.76)
Study 2 | VIIBRYD 40 mg/day | 231 | 31.9 (3.50) | -13.3 (0.90) | -2.5 (-4.4, -0.6)
 | Placebo | 232 | 32.0 (3.63) | -10.8 (0.90)
Study 3 | VIIBRYD 40 mg/day | 253 | 30.7 (3.3) | -16.1 (0.64) | -5.1 (-6.9, -3.3)
 | Placebo | 252 | 30.9 (3.3) | -11.0 (0.65)
Study 4 | VIIBRYD 20 mg/day* | 288 | 31.3 (3.5) | -17.3 (0.63) | -2.6 (-4.3, -0.8)
 | VIIBRYD 40 mg/day* | 284 | 31.2 (3.8) | -17.6 (0.65) | -2.8 (-4.6, -1.1)
 | Placebo | 281 | 31.4 (3.8) | -14.8 (0.62)

SD = standard deviation; SE = standard error; LS Mean = least-square mean; CI = confidence interval

a based on patients who took study medication and had baseline and postbaseline MADRS assessments
b difference (drug minus placebo) in least-square mean change from baseline to endpoint
* All VIIBRYD treatment dose groups remained statistically significant compared with placebo after adjusting for multiplicity

Baseline demographics information were generally similar across all treatment groups. Examination of population subgroups based on age (there were few patients over 65), gender and race did not reveal any clear evidence of differential responsiveness.

16 HOW SUPPLIED/STORAGE AND HANDLING

VIIBRYD (vilazodone HCl) tablets are supplied in the following configurations:

Tablet Strength | Tablet Color/Shape | Tablet Markings | Package Configuration | NDC Code
10 mg | pink, oval tablet | debossed with 10 on one side | Bottle / 30 count | 0456-1110-30
20 mg | orange, oval tablet | debossed with 20 on one side | Bottle / 30 count | 0456-1120-30
40 mg | blue, oval tablet | debossed with 40 on one side | Bottle / 30 count | 0456-1140-30

VIIBRYD (vilazodone HCl) Patient Starter Kits are supplied in the following configuration:

Package Configuration | Tablet Strength | Tablet Color/Shape | Tablet Markings | NDC Code
Patient Starter Kit containing seven 10 mg tablets, seven 20 mg tablets and sixteen 40 mg tablets | 10 mg | pink, oval tablet | debossed with 10 on one side | 0456-1100-31
 | 20 mg | orange, oval tablet | debossed with 20 on one side
 | 40 mg | blue, oval tablet | debossed with 40 on one side
Patient Starter Kit containing seven 10 mg tablets, twenty-three 20 mg tablets | 10 mg | pink, oval tablet | debossed with 10 on one side | 0456-1101-30
 | 20 mg | orange, oval tablet | debossed with 20 on one side

Store tablets at 25oC (77°F). Excursions permitted to 15oC - 30oC (59°F - 86°F) [see USP Controlled Room Temperature].

17 PATIENT COUNSELING INFORMATION

Advise the patient to read the FDA-approved patient labeling (Medication Guide).

Suicidal Thoughts and Behaviors

Advise patients and caregivers to look for the emergence of suicidality, especially early during treatment and when the dosage is adjusted up or down and instruct them to report such symptoms to the healthcare provider [see Boxed Warning and Warnings and Precautions (5.1)].

Dosage and Administration

Instruct patients to take VIIBRYD with food and to follow prescribed dosage instructions [see Dosage and Administration (2.1, 2.3, 2.4, 2.5)].

Serotonin Syndrome

Caution patients about the risk of serotonin syndrome, particularly with the concomitant use of VIIBRYD with other serotonergic drugs including triptans, tricyclic antidepressants, opioids, lithium, tryptophan, buspirone, amphetamines, and St. John’s Wort, and with drugs that impair metabolism of serotonin (in particular, MAOIs, both those intended to treat psychiatric disorders and also others, such as linezolid). Patients should contact their health care provider or report to the emergency room if they experience signs or symptoms of serotonin syndrome [see Warnings and Precautions (5.2) and Drug Interactions (7)].

Increased Risk of Bleeding

Inform patients about the concomitant use of VIIBRYD with aspirin, NSAIDs, other antiplatelet drugs, warfarin, or other anticoagulants because the combined use of drugs that interfere with serotonin reuptake (e.g., VIIBRYD) and these medications has been associated with an increased risk of bleeding. Advise them to inform their health care providers if they are taking or planning to take any prescription or over-the-counter medications that increase the risk of bleeding [see Warnings and Precautions (5.3)].

Activation of Mania/Hypomania

Advise patients and their caregivers to observe for signs of activation of mania/hypomania and instruct them to report such symptoms to the healthcare provider [see Warnings and Precautions (5.4)].

Discontinuation Syndrome

Advise patients not to abruptly discontinue VIIBRYD and to discuss any tapering regimen with their healthcare provider. Adverse reactions can occur when VIIBRYD is discontinued [see Warnings and Precautions (5.5)].

Seizures

Caution patients about using VIIBRYD if they have a history of a seizure disorder [see Warnings and Precautions (5.6)].

Sexual Dysfunction

Advise patients that use of VIIBRYD may cause symptoms of sexual dysfunction in both male and female patients. Inform patients that they should discuss any changes in sexual function and potential management strategies with their healthcare provider [see Warnings and Precautions (5.9)].

Allergic Reactions

Advise patients to notify their healthcare provider if they develop an allergic reaction such as rash, hives, swelling, or difficulty breathing [see Adverse Reactions (6.2)].

Concomitant Medications

Advise patients to inform their health care providers if they are taking, or plan to take any prescription or over-the-counter medications since there is a potential for interactions [see Drug Interactions (7.1)].

Pregnancy

- Advise pregnant women to notify their healthcare provider if they become pregnant or intend to become pregnant during treatment with VIIBRYD [see Use in Specific Populations (8.1)].
- Advise patients that VIIBRYD use late in pregnancy may lead to an increased risk for neonatal complications requiring prolonged hospitalization, respiratory support, tube feeding, and/or persistent pulmonary hypertension of the newborn (PPHN) [see Use in Specific Populations (8.1)].
- Advise patients that there is a pregnancy exposure registry that monitors pregnancy outcomes in women exposed to VIIBRYD during pregnancy[see Use in Specific Populations (8.1)].

Distributed by
AbbVie Inc.
1 N Waukegan Rd.
North Chicago, IL 60064

Licensed from Merck KGaA,
Darmstadt, Germany

© 2023 AbbVie. All rights reserved.
VIIBRYD and its design are trademarks of Allergan Sales, LLC, an AbbVie company.
20084716

MEDICATION GUIDE
VIIBRYD® (vī-brid)
(vilazodone hydrochloride)
Tablets, for oral use

What is the most important information I should know about VIIBRYD?
VIIBRYD may cause serious side effects, including:

- Increased risk of suicidal thoughts or actions in some children, adolescents, and young adults. VIIBRYD and other antidepressant medicines may increase suicidal thoughts or actions in some people 24 years of age and younger, especially within the first few months of treatment or when the dose is changed. VIIBRYD is not for use in children.
  - Depression or other serious mental illnesses are the most important causes of suicidal thoughts or actions. Some people may have a higher risk of having suicidal thoughts or actions. These include people who have (or have a family history of) depression, bipolar illness (also called manic-depressive illness) or have a history of suicidal thoughts or actions.

How can I watch for and try to prevent suicidal thoughts and actions?

- Pay close attention to any changes, especially sudden changes in mood, behavior, thoughts, or feelings, or if you develop suicidal thoughts or actions. This is very important when an antidepressant medicine is started or when the dose is changed.
- Call your healthcare provider right away to report new or sudden changes in mood, behavior, thoughts, or feelings.
- Keep all follow-up visits with your healthcare provider as scheduled. Call your healthcare provider between visits as needed, especially if you have concerns about symptoms.

Call your healthcare provider or get emergency medical help right away if you or your family member have any of the following symptoms, especially if they are new, worse, or worry you:

- attempts to commit suicide
- acting aggressive, being angry or violent
- new or worse depression
- panic attacks
- new or worse irritability
- an extreme increase in activity or talking (mania)

- acting on dangerous impulses
- thoughts about suicide or dying
- new or worse anxiety
- feeling agitated or restless
- trouble sleeping (insomnia)
- other unusual changes in behavior or mood

What is VIIBRYD?
VIIBRYD is a prescription medicine used to treat a certain type of depression called Major Depressive Disorder (MDD) in adults.
It is not known if VIIBRYD is safe and effective for use in children for the treatment of MDD.

Who should not take VIIBRYD?
Do not take VIIBRYD if you:

- take a Monoamine Oxidase Inhibitor (MAOI)
- have stopped taking an MAOI in the last 14 days
- are being treated with the antibiotic linezolid or intravenous methylene blue

Ask your healthcare provider or pharmacist if you are not sure if you take an MAOI, including the antibiotic linezolid or intravenous methylene blue.
Do not start taking an MAOI for at least 14 days after you stop treatment with VIIBRYD.

Before taking VIIBRYD, tell your healthcare provider about all your medical conditions, including if you:

- have or have a family history of suicide, depression, bipolar disorder, mania or hypomania
- have or had bleeding problems
- have or had seizures or convulsions
- have high pressure in the eye (glaucoma)
- have or had seizures or convulsions
- have low sodium levels in your blood
- drink alcohol
- are pregnant or plan to become pregnant. Taking VIIBYRD late in pregnancy may lead to an increased risk of certain problems in your newborn. Talk to your healthcare provider about the risks to your baby if you take VIIBRYD during pregnancy. Tell your healthcare provider right away if you become pregnant or think you may be pregnant during treatment with VIIBRYD.
  - There is a pregnancy registry for females who are exposed to VIIBRYD pregnancy. The purpose of the registry is to collect information about the health of females exposed to VIIBRYD and their baby. If you become pregnant during treatment with VIIBRYD, talk to your healthcare provider about registering with the National Pregnancy Registry for Antidepressants. You can register by calling 1-844-405-6185 or visiting online at https://womensmentalhealth.org/research/pregnancyregistry/antidepressants.
- are breastfeeding or plan to breastfeed. It is not known if VIIBRYD passes into breast milk. Talk to your healthcare provider about the best way to feed your baby during treatment with VIIBRYD.

Tell your healthcare provider about all the medicines you take, including prescription and over-the-counter medicines, vitamins, and herbal supplements.
VIIBRYD and some medicines may affect each other causing possible serious side effects. VIIBRYD may affect the way other medicines work and other medicines may affect the way VIIBRYD works.
Especially tell your healthcare provider if you take:

- MAOIs
- medicines used to treat migraine headaches known as triptans
- tricyclic antidepressants
- lithium
- tramadol, fentanyl, meperidine, methadone, or other opioids
- tryptophan
- buspirone
- amphetamines
- St. John’s Wort
- medicines that can affect blood clotting such as aspirin, nonsteroidal anti-inflammatory drugs (NSAIDs) and warfarin
- diuretics
- medicines used to treat mood, anxiety, psychotic or thought disorders, including selective serotonin reuptake inhibitors (SSRIs) and serotonin norepinephrine reuptake inhibitors (SNRIs)

Ask your healthcare provider if you are not sure if you are taking any of these medicines. Your healthcare provider can tell you if it is safe to take VIIBRYD with your other medicines.
Do not start or stop any other medicines during treatment with VIIBRYD without talking to your healthcare provider first. Stopping VIIBRYD suddenly may cause you to have serious side effects. See, “What are the possible side effects of VIIBRYD?”
Know the medicines you take. Keep a list of them to show to your healthcare provider and pharmacist when you get a new medicine.

How should I take VIIBRYD?

- Take VIIBRYD exactly as your healthcare provider tell you to. Do not change your dose or stop taking VIIBRYD without first talking to your healthcare provider.
- Your healthcare provider may need to change the dose of VIIBRYD until it is the right dose for you.
- Take VIIBRYD 1 time each day with food.
- If you miss a dose of VIIBRYD, take the missed dose as soon as you remember. If it is almost time for the next dose, skip the missed dose and take your next dose at the regular time. Do not take two doses of VIIBRYD at the same time.
- If you take too much VIIBRYD, call your healthcare provider or poison control center at 1-800-222-1222 right away, or get emergency treatment right away.

What should I avoid while taking VIIBRYD?

- Do not drive, operate heavy machinery, or do other dangerous activities until you know how VIIBRYD affects you. VIIBRYD can cause sleepiness or may affect your ability to make decisions, think clearly, or react quickly.
- Avoid drinking alcohol during treatment with VIIBRYD.

What are the possible side effects of VIIBRYD?
VIIBRYD may cause serious side effects, including:

- See, “What is the most important information I should know about VIIBRYD?”
- Serotonin Syndrome. A potentially life-threatening problem called serotonin syndrome can happen when VIIBRYD is taken with certain other medicines. See, “Who should not take VIIBRYD?” Stop taking VIIBRYD and call your healthcare provider or go to the nearest hospital emergency room right away if you have any of the following signs and symptoms of serotonin syndrome:

- agitation
- confusion
- fast heart beat
- dizziness
- flushing
- tremors, stiff muscles, or muscle twitching
- seizures

- seeing or hearing things that are not real (hallucinations)
- coma
- blood pressure changes
- sweating
- high body temperature (hyperthermia)
- loss of coordination
- nausea, vomiting, diarrhea

- Increased risk of bleeding. Taking VIIBRYD with aspirin, non-steroidal anti-inflammatory drugs (NSAIDs), warfarin or blood thinners may add to this risk. Tell your healthcare provider right away about any unusual bleeding or bruising.
- Mania or hypomania (manic episodes) in people who have a history of bipolar disorder. Symptoms may include:

- greatly increased energy
- racing thoughts
- unusually grand ideas
- talking more or faster than usual

- severe trouble sleeping
- reckless behavior
- excessive happiness or irritability

- Discontinuation syndrome. Suddenly stopping VIIBRYD may cause you to have serious side effects. Your healthcare provider may want to decrease your dose slowly. Symptoms may include:

- nausea
- changes in your mood
- irritability and agitation
- dizziness
- electric shock sensation (paresthesia)
- anxiety
- confusion

- sweating
- headache
- tiredness
- problems sleeping
- hypomania
- ringing in your ears (tinnitus)
- seizures

- Seizures (convulsions).
- Eye problems (angle-closure glaucoma): VIIBRYD may cause a certain type of eye problem called angle-closure glaucoma. Call your healthcare provider if you have changes in your vision or eye pain.
- Low sodium levels in your blood (hyponatremia). Low sodium levels in your blood may be serious and may cause death. Elderly people may be at greater risk for this. Signs and Symptoms of low sodium levels in your blood may include:

- headache
- memory changes
- weakness and unsteadiness on your feet which can lead to falls

- difficulty concentrating
- confusion

In severe or more sudden cases, signs and symptoms include:

- hallucinations (seeing or hearing things that are not real)
- seizures
- respiratory arrest

- fainting
- coma
- death

- Sexual problems (dysfunction). Taking selective serotonin reuptake inhibitors (SSRIs), including VIIBRYD, may cause sexual problems.
  Symptoms in males may include:

- delayed ejaculation or inability to have an ejaculation

- decreased sex drive

- problems getting or keeping an erection

Symptoms in females may include:

- decreased sex drive

- delayed orgasm or inability to have an orgasm

Talk to your healthcare provider if you develop any changes in your sexual function or if you have any questions or concerns about sexual problems during treatment with VIIBRYD. There may be treatments your healthcare provider can suggest.
The most common side effects of VIIBRYD include diarrhea, nausea or vomiting, trouble sleeping.
These are not all the possible side effects of VIIBRYD.
Call your doctor for medical advice about side effects. You may report side effects to FDA at 1-800-FDA-1088.

How should I store VIIBRYD?

- Store VIIBRYD at room temperature between 68°F to 77°F (20°C to 25°C).
- Keep VIIBRYD and all medicines out of the reach of children.

General information about the safe and effective use of VIIBRYD.
Medicines are sometimes prescribed for purposes other than those listed in a Medication Guide. Do not use VIIBRYD for a condition for which it was not prescribed. Do not give VIIBRYD to other people, even if they have the same symptoms that you have. It may harm them. You may ask your healthcare provider or pharmacist for information about VIIBRYD that is written for healthcare professionals.

What are the ingredients in VIIBRYD?
Active ingredient: vilazodone hydrochloride
Inactive ingredients: colloidal silicon dioxide, lactose monohydrate, magnesium stearate, microcrystalline cellulose, polyethylene glycol, polyvinyl alcohol, talc, titanium dioxide, FD&C Blue #1 (40 mg only), FD&C Red #40 (10 mg only) and FD&C Yellow #6 (20 mg only)

Distributed by:
AbbVie Inc.
1 N Waukegan Rd.
North Chicago, IL 60064
Licensed from Merck KGaA, Darmstadt, Germany
© 2024 AbbVie. All rights reserved.
VIIBRYD and its design are trademarks of Allergan Sales, LLC, an AbbVie company.
For more information about VIIBRYD call 1-800-678-1605.

This Medication Guide has been approved by the U.S. Food and Drug Administration. Revised: 4/2024

20084716

PRINCIPAL DISPLAY PANEL

NDC 0456-1110-30

RX only
30 Tablets
Viibryd®
vilazodone HCl
tablets
10 mg
Dispense the accompanying
Medication Guide to each patient

PRINCIPAL DISPLAY PANEL

NDC 0456-1120-30

Rx only
30 Tablets
Viibryd®
vilazodone HCl
tablets
20 mg
Dispense the accompanying
Medication Guide to each patient

PRINCIPAL DISPLAY PANEL

NDC 0456-1140-30

RX only
30 Tablets
Viibryd®
vilazodone HCl
tablets
40 mg
Dispense the accompanying
Medication Guide to each patient

PRINCIPAL DISPLAY PANEL

Rx only NDC 0456-1100-31
Viibryd®

PRINCIPAL DISPLAY PANEL

Rx only NDC 0456-1101-30
Viibryd®